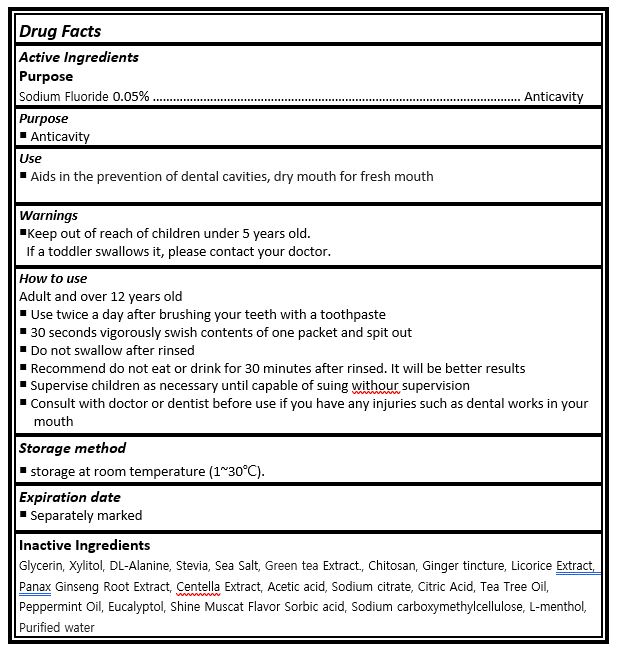 DRUG LABEL: Lartt mouthwash
NDC: 61284-0014 | Form: LIQUID
Manufacturer: ECOWORLDPHARM CO.,LTD
Category: otc | Type: HUMAN OTC DRUG LABEL
Date: 20240405

ACTIVE INGREDIENTS: SODIUM FLUORIDE 0.05 g/100 mL
INACTIVE INGREDIENTS: XYLITOL; PANAX GINSENG ROOT OIL; WATER

Drug Facts

ACTIVE INGREDIENT

sodium fluoride

INACTIVE INGREDIENT

Glycerin, Xylitol, DL-Alanine, Stevia, Sea Salt, Green tea Extract., Chitosan, Ginger tincture, Licorice Extract, Panax Ginseng Root Extract, Centella Extract, Acetic acid, Sodium citrate, Citric Acid, Tea Tree Oil, Peppermint Oil, Eucalyptol, Shine Muscat Flavor Sorbic acid, Sodium carboxymethylcellulose, L-menthol, Purified water

PURPOSE

Anticavity

KEEP OUT OF REACH OF THE CHILDREN

INDICATIONS AND USAGE

Adult and over 12 years old

¡ Use twice a day after brushing your teeth with a toothpaste

¡ 30 seconds vigorously swish contents of one packet and spit out

¡ Do not swallow after rinsed

¡ Recommend do not eat or drink for 30 minutes after rinsed. It will be better results

¡ Supervise children as necessary until capable of suing withour supervision

¡ Consult with doctor or dentist before use if you have any injuries such as dental works in your mouth

WARNINGS

if more than used for rinsing is accidentally swallowed, get medical help or contact a Poison Control Center right away

DOSAGE AND ADMINISTRATION

for dental use only